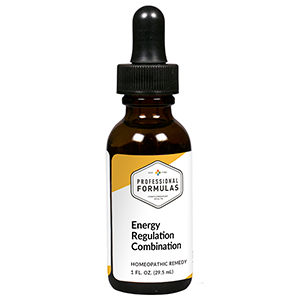 DRUG LABEL: Energy Regulation Combination
NDC: 63083-9308 | Form: LIQUID
Manufacturer: Professional Complementary Health Formulas
Category: homeopathic | Type: HUMAN OTC DRUG LABEL
Date: 20190815

ACTIVE INGREDIENTS: SODIUM CARBONATE 3 [hp_X]/29.5 mL; PULSATILLA MONTANA WHOLE 6 [hp_X]/29.5 mL; CALCIUM SULFIDE 10 [hp_X]/29.5 mL; SULFUR 10 [hp_X]/29.5 mL; CREATINE 12 [hp_X]/29.5 mL; 3-HYDROXY-1-METHYLGUANINE 12 [hp_X]/29.5 mL
INACTIVE INGREDIENTS: ALCOHOL; WATER

R308

ACTIVE INGREDIENTS

Natrum carbonicum 3X
Pulsatilla 6X
Hepar sulphuris calcareum 10X
Sulphur 10X
Creatine 12X
Guanine 12X

QUESTIONS

Professional Formulas

PO Box 2034 Lake Oswego, OR 97035

INDICATIONS

For the temporary relief of exhaustion, fatigue, or debility.*

PURPOSE

*Claims based on traditional homeopathic practice, not accepted medical evidence. Not FDA evaluated.

WARNINGS

Consult a doctor if condition worsens or if symptoms persist. Keep out of the reach of children. In case of overdose, get medical help or contact a poison control center right away. If pregnant or breastfeeding, ask a healthcare professional before use.

Keep out of the reach of children.

PREGNANCY OR BREAST FEEDING

If pregnant or breastfeeding, ask a healthcare professional before use.

DIRECTIONS

Place drops under tongue 30 minutes before/after meals. Adults and children 12 years and over: Take 10 drops up to 3 times per day. Consult a physician for use in children under 12 years of age.

OTHER INFORMATION

Tamper resistant. If seal is broken, do not use. After opening, close container tightly and store at room temperature away from heat.

INACTIVE INGREDIENTS

40% ethanol, purified water.

LABEL

Est 1985

Professional Formulas

Complementary Health

Energy Regulation Combination

Homeopathic Remedy

1 FL. OZ. (29.5 mL)